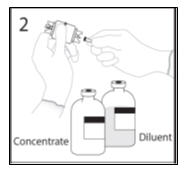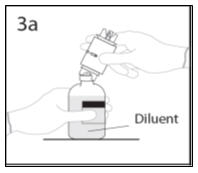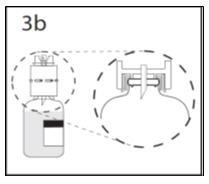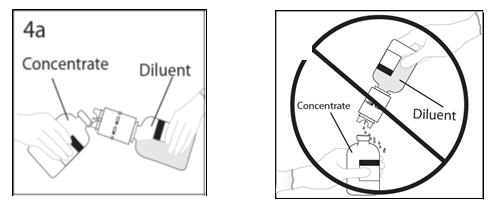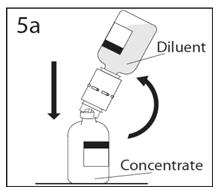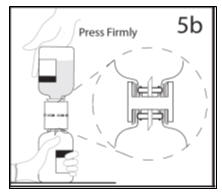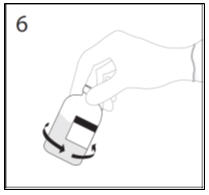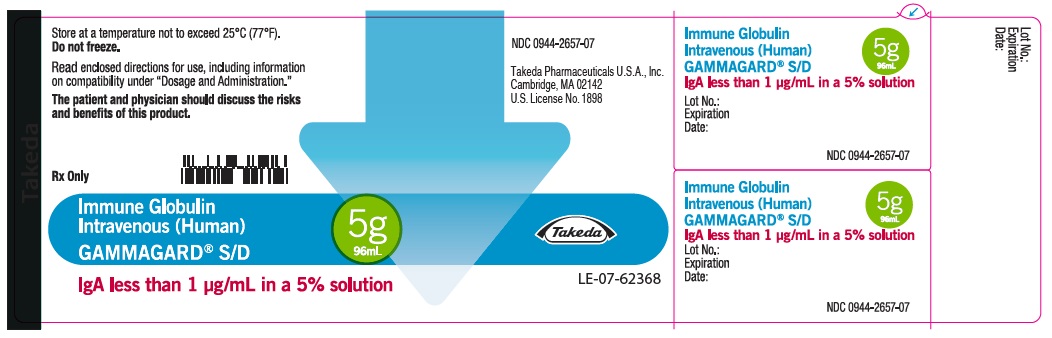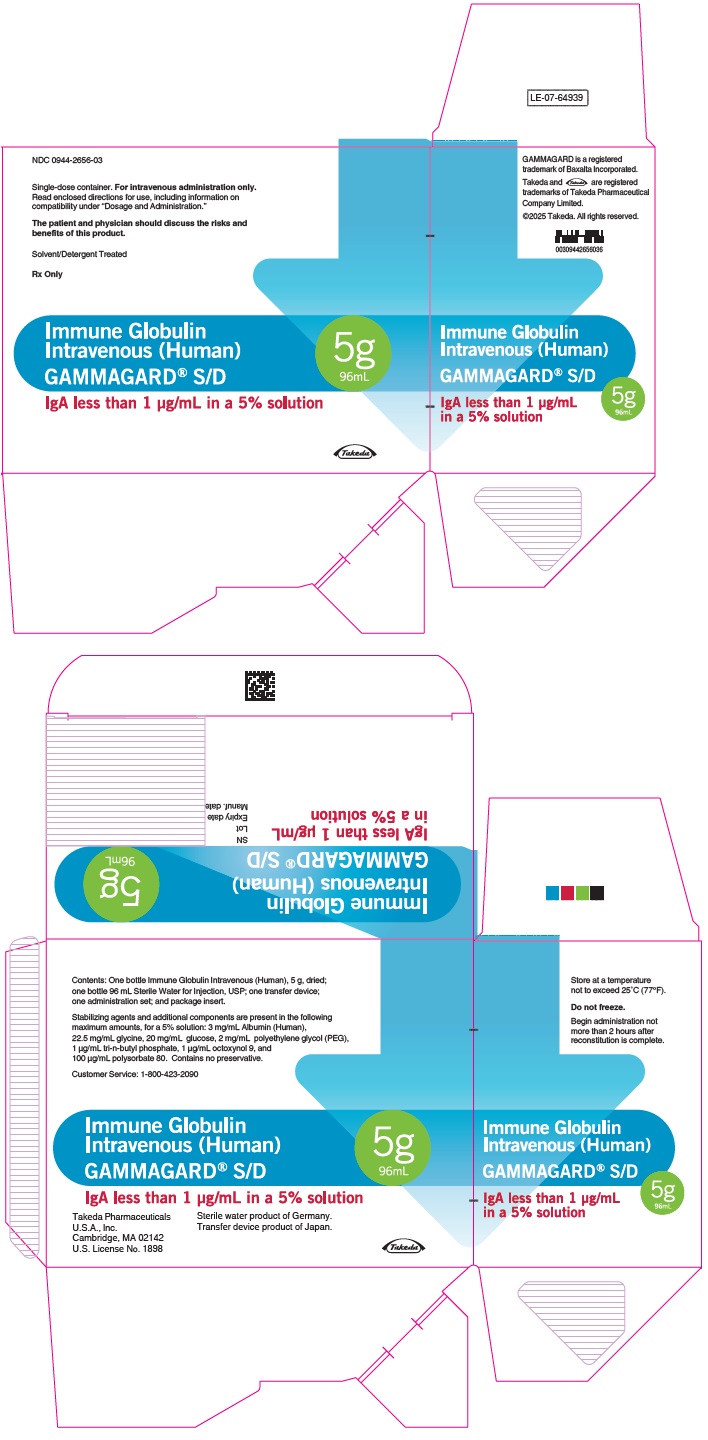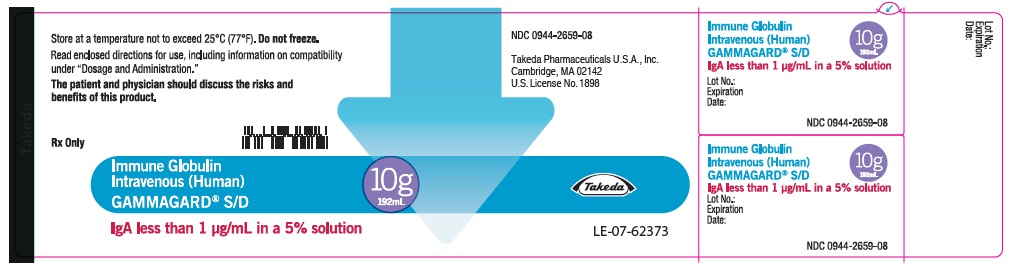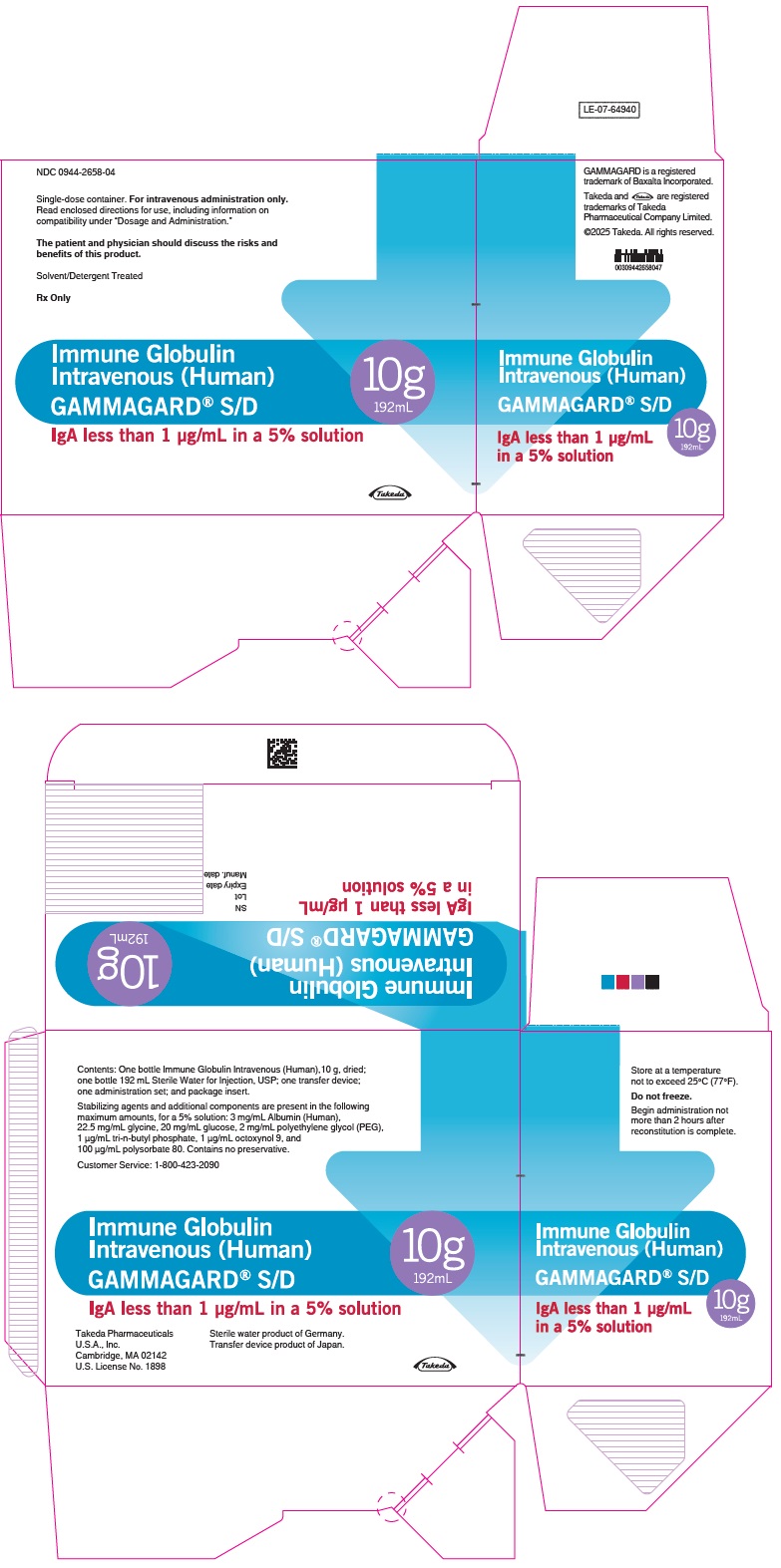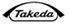 DRUG LABEL: GAMMAGARD
NDC: 0944-2656 | Form: KIT | Route: INTRAVENOUS
Manufacturer: Takeda Pharmaceuticals America, Inc.
Category: other | Type: PLASMA DERIVATIVE
Date: 20251125

ACTIVE INGREDIENTS: HUMAN IMMUNOGLOBULIN G 50 mg/1 mL
INACTIVE INGREDIENTS: ALBUMIN HUMAN; GLYCINE; ANHYDROUS DEXTROSE; POLYETHYLENE GLYCOL, UNSPECIFIED; TRI-N-BUTYL PHOSPHATE; OCTOXYNOL-9; POLYSORBATE 80; SODIUM CHLORIDE; WATER 96 mL/96 mL; WATER 96 mL/96 mL

HIGHLIGHTS OF PRESCRIBING INFORMATION

These highlights do not include all the information needed to use GAMMAGARD S/D safely and effectively. See full prescribing information for GAMMAGARD S/D
GAMMAGARD® S/D, Immune Globulin Intravenous (Human)
IgA less than 1 microgram per mL in a 5% Solution
Initial U.S. Approval: 1994

WARNING: THROMBOSIS, RENAL DYSFUNCTION, and ACUTE RENAL FAILURE

See full prescribing information for complete boxed warning.

- Thrombosis may occur with immune globulin products, including GAMMAGARD S/D. Risk factors may include advanced age, prolonged immobilization, hypercoagulable conditions, history of venous or arterial thrombosis, use of estrogens, indwelling vascular catheters, hyperviscosity and cardiovascular risk factors. (5.3)
- Renal dysfunction, acute renal failure, osmotic nephrosis, and death may occur in predisposed patients with immune globulin intravenous (IGIV) products, including GAMMAGARD S/D. Renal dysfunction and acute failure occur more commonly with IGIV products containing sucrose. GAMMAGARD S/D does not contain sucrose. (5.2)
- For patients at risk of thrombosis, administer GAMMAGARD S/D at the minimum dose and infusion rate practicable. Ensure adequate hydration in patients before administration. Monitor for signs and symptoms of thrombosis and assess blood viscosity in patients at risk of hyperviscosity. (5.3)

1 INDICATIONS AND USAGE

GAMMAGARD S/D is an Immune Globulin Intravenous (Human) indicated for:

- Treatment of primary immunodeficiency (PI) in adults and pediatric patients two years of age or older. (1)
- Prevention of bacterial infections in hypogammaglobulinemia and/or recurrent bacterial infections associated with B-cell chronic lymphocytic leukemia (CLL). (1)
- Prevention and/or control of bleeding in adult chronic idiopathic thrombocytopenic purpura (ITP) patients. (1)
- Prevention of coronary artery aneurysms associated with Kawasaki syndrome in pediatric patients. (1)

2 DOSAGE AND ADMINISTRATION

Intravenous Use Only

Indication | Recommended Dosage | Duration
PI (2.2) | 300-600 mg/kg | Every 3 to 4 weeks
CLL (2.2) | 400 mg/kg | Every 3 to 4 weeks
ITP (2.2) | 1g/kg | Maximal 3 doses on alternate days
Kawasaki Syndrome (2.2) | Single 1g/kg or 400 mg/kg for 4 consecutive days | Begin within 7 days of onset of fever [Administer concomitant aspirin therapy: 80-100 mg/kg/day in four divided doses]

3 DOSAGE FORMS AND STRENGTHS

Freeze-dried preparation containing 5 g or 10 g IgG. (3)

4 CONTRAINDICATIONS

History of anaphylactic or severe systemic hypersensitivity reactions to the administration of GAMMAGARD S/D <1µg/mL IgA in a 5 % solution. (4)

5 WARNINGS AND PRECAUTIONS

- IgA-deficient patients with antibodies to IgA are at greater risk of severe hypersensitivity reactions and anaphylactic reactions. (5.1)
- Monitor renal function, including blood urea nitrogen, serum creatinine, and urine output in patients at risk of acute renal failure. (5.2)
- Thrombosis may occur. Monitor for signs and symptoms of thrombosis and assess blood viscosity for those at risk for hyperviscosity. (5.3)
- Aseptic Meningitis Syndrome (AMS) has been reported (5.4)
- Hemolytic anemia can develop. Monitor patients for clinical signs and symptoms of hemolysis and hemolytic anemia. (5.5)
- Monitor patients for pulmonary adverse reactions (transfusion-related acute lung injury, TRALI). (5.6)
- GAMMAGARD S/D is made from human blood, it may carry a risk of transmitting infectious agents, e.g., viruses, the variant Creutzfeldt-Jakob disease (vCJD) agent, and theoretically, the Creutzfeldt-Jakob disease (CJD) agent. (5.7)
- Hyperproteinemia, increased serum viscosity, and alterations in serum sodium levels may occur. (5.8)

6 ADVERSE REACTIONS

- The most common adverse reactions observed in ≥ 5% of patients during the clinical trials were headache, nausea, chills, fatigue, pyrexia, upper abdominal pain, diarrhea, back pain, infusion site pain, hyperhidrosis and flushing. (6.1)
- The most serious adverse reactions reported postmarketing include renal failure, thrombotic events (myocardial infarction, cerebrovascular accidents, and pulmonary embolism), anaphylactic shock, aseptic meningitis and hemolysis. (6.2)

To report SUSPECTED ADVERSE REACTIONS, contact Takeda Pharmaceuticals U.S.A., Inc. at 1-877-TAKEDA-7 (1-877-825-3327) or FDA at 1-800-FDA-1088 or www.fda.gov/medwatch.

7 DRUG INTERACTIONS

Passive transfer of antibodies may interfere with the immune response to live vaccines, such as measles, mumps, and rubella.

8 USE IN SPECIFIC POPULATIONS

Geriatric: Do not exceed the recommended dose. Infuse GAMMAGARD S/D at the minimum infusion rate practicable. (8.5)

FULL PRESCRIBING INFORMATION

WARNING: THROMBOSIS, RENAL DYSFUNCTION, and ACUTE RENAL FAILURE

■ Thrombosis may occur with immune globulin products, including GAMMAGARD S/D. Risk factors may include advanced age, prolonged immobilization, hypercoagulable conditions, history of venous or arterial thrombosis, use of estrogens, indwelling vascular catheters, hyperviscosity and cardiovascular risk factors. Thrombosis may occur in the absence of known risk factors [see Warnings and Precautions (5.3), Patient Counseling Information (17)].
● Renal dysfunction, acute renal failure, osmotic nephrosis, and death may occur in predisposed patients who receive immune globulin intravenous (IGIV) products, including GAMMAGARD S/D. Patients predisposed to renal dysfunction include those with any degree of pre-existing renal insufficiency, diabetes mellitus, age above 65, volume depletion, sepsis, paraproteinemia, or patients receiving known nephrotoxic drugs. Renal dysfunction and acute renal failure occur more commonly in patients receiving IGIV product containing sucrose. GAMMAGARD S/D does not contain sucrose. (5.2)
● For patients at risk of thrombosis, administer GAMMAGARD S/D at the minimum dose and infusion rate practicable. Ensure adequate hydration in patients before administration. Monitor for signs and symptoms of thrombosis and assess blood viscosity in patients at risk of hyperviscosity [see Dosage and Administration (2.3) and Warnings and Precautions (5.3)].

1 INDICATIONS AND USAGE

Primary Immunodeficiency (PI)

GAMMAGARD S/D is indicated for the treatment of primary immunodeficiency (PI) associated with defects in humoral immunity, in adults and children two years and older. This includes, but is not limited to, congenital agammaglobulinemia, common variable immunodeficiency, Wiskott-Aldrich syndrome, and severe combined immunodeficiencies.^1,2,3

B-cell Chronic Lymphocytic Leukemia (CLL)

GAMMAGARD S/D is indicated for prevention of bacterial infections in patients with hypogammaglobulinemia and/or recurrent bacterial infections associated with B-cell chronic lymphocytic leukemia (CLL).^4

Idiopathic Thrombocytopenic Purpura (ITP)

GAMMAGARD S/D is indicated for the treatment of adult chronic idiopathic thrombocytopenic purpura to increase platelet count and to prevent and/or to control bleeding.

Kawasaki Syndrome

GAMMAGARD S/D is indicated for the prevention of coronary artery aneurysms associated with Kawasaki syndrome in pediatric patients.^5

2 DOSAGE AND ADMINISTRATION

For Intravenous Use Only

2.1 Preparation and Handling

Instructions for Reconstitution:

Allow GAMMAGARD S/D and diluent to reach room temperature before reconstitution and administration if refrigerated.

Reconstitution:

1. Remove caps from concentrate and diluent bottles to expose central portion of rubber stoppers and cleanse stoppers with germicidal solution.

- To make a 5% solution: Use the full volume of the diluent bottle
- To make a 10% solution: Remove half of the volume of the diluent bottle

Table 1 indicates the volume of diluent to be removed from the vial before attaching the transfer device to produce a 10% concentration. Using aseptic technique, withdraw the unnecessary volume of diluent using a sterile hypodermic syringe and needle. Discard the filled syringe into a suitable puncture proof container (sharps container).

Table 1 Diluent Volume to be Removed to Produce a 10% Solution
Concentration | 5 g bottle | 10 g bottle
5% | Do not remove any diluent for reconstitution of 5% Solution
10% | 48 mL | 96 mL

2. Remove spike cap from one end of the transfer device. Do not touch spike.
3a. Place the diluent bottle on a flat surface and hold the bottle to prevent slipping. Use exposed end of transfer device to spike diluent bottle perpendicularly through center of the stopper. CAUTION: Failure to insert spike into center of the stopper may result in dislodging of the stopper.
3b. Ensure that the collar collapses fully into the device by pushing down on the transfer device firmly. While holding onto transfer device, remove remaining spike cover from the other end of the transfer device. Do not touch spike.
4. Hold diluent bottle with attached transfer device at an angle to the concentrate bottle to prevent spilling the diluent. Note: Do not hold diluent bottle upside down, for this can lead to diluent spillage.
5a. Spike concentrate bottle through center of the stopper while quickly inverting the diluent bottle to minimize spilling out diluent. CAUTION: Failure to insert the spike into the center of the stopper may result in dislodging of the stopper and loss of vacuum.
5b. Ensure that the collar collapses fully into the device by pushing down on the diluent bottle firmly.
6. After transfer of diluent is complete, remove transfer device and empty diluent bottle. Immediately swirl the concentrate bottle gently to thoroughly mix contents. Repeat gentle rotation as long as undissolved product is observed. CAUTION: Do not shake. Avoid foaming. Discard transfer device after single use per local guidelines.

- Visually inspect parenteral drug product for particulate matter and discoloration prior to administration. Reconstituted GAMMAGARD S/D is a clear to slightly opalescent and colorless to pale yellow solution. Do not use if particulate matter and/or discoloration is observed.
- Follow directions for use which accompany the administration set provided. If another administration set is used, ensure that the set contains a similar filter.
- Begin administration as soon as possible within 2 hours if reconstitution is performed aseptically outside of a sterile laminar air flow hood.
- Administer within 24 hours if reconstitution is performed aseptically inside of a sterile laminar flow hood and stored in the original glass container or pooled into ViaFlex bags under constant refrigeration (2°C to 8°C). Record the date and time of reconstitution/pooling. Discard partially used vials.

2.2 Dose

Primary Immunodeficiency (PI)

The recommended dose of GAMMAGARD S/D for patients with PI is 300-600 mg/kg infused at 3 to 4 week intervals.^1,2,6 Adjust dose according to the clinical response; the frequency and dose of immunoglobulin may vary from patient to patient. No randomized controlled clinical trials are available to determine an optimum target trough serum IgG level.

B-cell Chronic Lymphocytic Leukemia (CLL)

The recommended dose of GAMMAGARD S/D for patients with hypogammaglobulinemia and/or recurrent bacterial infections due to B-cell CLL is 400 mg/kg body weight infused at every 3 to 4 week intervals.^4

Idiopathic Thrombocytopenic Purpura (ITP)

The recommended dose of GAMMAGARD S/D for patients with chronic ITP is 1 g/kg. The need for additional doses can be determined by clinical response and platelet count. Up to three separate doses may be given on alternate days if required.

Kawasaki Syndrome

The recommended dose of GAMMAGARD S/D for patients with Kawasaki syndrome is either a single 1 g/kg dose or a dose of 400 mg/kg for four consecutive days beginning within seven days of the onset of fever, administered concomitantly with appropriate aspirin therapy (80-100 mg/kg/day in four divided doses).^5,7,8

Measles Exposure

If a patient has been exposed to measles, it may be prudent to administer an extra dose of GAMMAGARD S/D as soon as possible and within 6 days of exposure. A dose of 400 mg/kg should provide a serum level > 240 mIU/mL of measles antibodies for at least two weeks.

If a patient is at risk of future measles exposure and receives a dose of less than 530 mg/kg every 3-4 weeks, the dose should be increased to at least 530 mg/kg. This should provide a serum level of 240 mIU/mL of measles antibodies for at least 22 days after infusion.

2.3 Administration

Administer GAMMAGARD S/D as soon after reconstitution as possible and administer the reconstituted material at room temperature.

The recommended initial 5% solution infusion rate is 0.5 mL/kg/hour. The infusion rate may be gradually increased to a maximum rate of 4 mL/kg/hour as tolerated for patients with no history of adverse reactions to IGIV and no significant risk factors for renal dysfunction or thrombotic complications. Patients who tolerate the 5% concentration at 4 mL/kg/hour can be infused with the 10% concentration starting at 0.5 mL/kg/hour. The rate can be increased gradually up to a maximum of 8 mL/kg/hour if no adverse effects occur.^9

Monitor patient vital signs throughout the infusion. Certain adverse reactions such as headaches, flushing and changes in pulse rate and blood pressure may be related to the rate of infusion. Slow or stop the infusion if adverse reactions occur. If symptoms subside promptly, the infusion may be resumed at a lower rate that does not result in reoccurrence of the symptoms.

It is recommended that, if possible, the antecubital veins are used, especially for 10% solutions, to reduce the likelihood of discomfort at the infusion site [see Adverse Reactions (6)].

Adverse reactions may occur more frequently in patients who receive human IGIV for the first time, upon switching brands, or if there has been a long hiatus since the previous infusion. In such cases, start at a lower rate and gradually increase as tolerated.

There are no prospective studies demonstrating that any concentration or rate of infusion is completely safe. However, the risk may be decreased at lower rates of infusion.^10 For patients who are judged to be at risk of renal dysfunction or thrombotic complications, administer GAMMAGARD S/D at the minimum practicable rate of infusion and gradually titrate up to a more conservative maximal rate of less than 3.3 mg/kg/min (< 2mL/kg/hour of a 10% or < 4mL/kg/hour of a 5% solution) [see Warnings and Precautions (5.3)].

3 DOSAGE FORMS AND STRENGTHS

GAMMAGARD S/D with an IgA concentration of less than 1 µg/mL is a freeze-dried preparation containing 5 g or 10 g IgG in a single-use vial.

4 CONTRAINDICATIONS

GAMMAGARD S/D is contraindicated in patients who have a history of anaphylactic or severe systemic hypersensitivity reactions to the administration of GAMMAGARD S/D with <1µg/mL IgA in a 5 % solution.

5 WARNINGS AND PRECAUTIONS

5.1 Hypersensitivity

Severe hypersensitivity reactions and anaphylactic reactions with a fall in blood pressure have occurred in patients receiving GAMMAGARD S/D, including patients who tolerated previous treatments with GAMMAGARD S/D, even though it contains low levels of IgA. If hypersensitivity reaction develops, discontinue GAMMAGARD S/D infusion immediately and institute appropriate treatment.

This product has an IgA concentration less than 1 µg/mL. Preparations depleted of IgA (0.4 to 2.9 µg/mL) were shown to be better tolerated by a limited number of patients who reacted to IGIV preparations with higher IgA concentrations. However, the concentration of IgA that will not provoke a reaction is not known, and therefore all IGIV preparations carry the risk of inducing an anaphylactic reaction to IgA. In such instances, a risk of anaphylaxis may exist despite the fact that GAMMAGARD S/D, IgA < 1 µg/mL, contains < 1 µg/mL IgA.

5.2 Renal Dysfunction/Failure

Acute renal failure has been reported in association with GAMMAGARD S/D. Acute renal dysfunction/failure, acute tubular necrosis, proximal tubular nephropathy, osmotic nephrosis and death have been reported in patients receiving IGIV, particularly those products containing sucrose.^10 GAMMAGARD S/D does not contain sucrose.

Ensure that patients are not volume depleted prior to the initiation of the infusion of GAMMAGARD S/D. In patients who are at risk of developing renal dysfunction, because of pre-existing renal insufficiency or predisposition to acute renal failure (such as diabetes mellitus, age greater than 65, volume depletion, sepsis, paraproteinemia, or patients receiving known nephrotoxic drugs, etc.), administer GAMMAGARD S/D at an infusion rate less than 4 mL/kg/hour (< 3.3 mg IG/kg/min) for a 5% solution or at a rate less than 2 mL/kg/hour (< 3.3 mg IG/kg/min) for a 10 % solution [see Dosage and Administration (2)].

Monitor renal function and urine output in patients judged to be at increased risk for developing acute renal failure. Assess renal function, including measurement of blood urea nitrogen (BUN) and serum creatinine, before the initial infusion of GAMMAGARD S/D and again at appropriate intervals thereafter. If renal function deteriorates, consider discontinuation of GAMMAGARD S/D.

5.3 Thrombosis

Thrombosis may occur following treatment with immune globulin products, including GAMMAGARD S/D. Risk factors may include advanced age, prolonged immobilization, hypercoagulable conditions, history of venous or arterial thrombosis, use of estrogens, indwelling central vascular catheters, hyperviscosity, and cardiovascular risk factors. Thrombosis may occur in the absence of known risk factors.

Consider baseline assessment of blood viscosity in patients at risk for hyperviscosity, including those with cryoglobulins, fasting chylomicronemia/markedly high triacylglycerols (triglycerides), or monoclonal gammopathies. For patients at risk of thrombosis, administer GAMMAGARD S/D at the minimum dose and infusion rate practicable. Ensure adequate hydration in patients before administration. Monitor for signs and symptoms of thrombosis and assess blood viscosity in patients at risk for hyperviscosity [see Boxed Warning, Dosage and Administration (2.3), Patient Counseling Information (17)].

5.4 Aseptic Meningitis Syndrome (AMS)

AMS has been reported to occur in association with immune globulin therapy, including GAMMAGARD S/D. AMS may occur more frequently in female patients. Discontinuation of immune globulin treatment has resulted in remission of AMS within several days without sequelae. The syndrome of AMS usually begins within several hours to two days following immune globulin treatment.

AMS is characterized by the following symptoms and signs: severe headache, nuchal rigidity, drowsiness, fever, photophobia, painful eye movements, nausea, and vomiting. Cerebrospinal fluid (CSF) studies are frequently positive with pleocytosis up to several thousand cells per cubic mm, predominantly from the granulocytic series, and with elevated protein levels up to several hundred mg/dL, but negative culture results. Conduct a thorough neurological examination on patients exhibiting such symptoms and signs, including CSF studies, to rule out other causes of meningitis.

5.5 Hemolysis

Hemolytic anemia can develop subsequent to IGIV therapy, including GAMMAGARD S/D^11 [see Adverse Reactions (6.2)]. GAMMAGARD S/D contains blood group antibodies which may act as hemolysins and induce in vivo coating of red blood cells (RBC) with immunoglobulin, causing a positive direct antiglobulin reaction and, rarely, hemolysis. Acute intravascular hemolysis has been reported, and delayed hemolytic anemia can develop subsequent to IGIV therapy due to enhanced RBC sequestration [see Adverse Reactions (6.2)].

Monitor patients for clinical signs and symptoms of hemolysis. If signs or symptoms of hemolysis are present after GAMMAGARD S/D infusion, perform appropriate confirmatory laboratory testing.

5.6 Transfusion-Related Acute Lung Injury (TRALI)

Non-cardiogenic pulmonary edema (TRALI) has been reported in patients following the administration of immunoglobulin products, including GAMMAGARD S/D therapy [see Adverse Reactions (6.2)]. TRALI is characterized by severe respiratory distress, pulmonary edema, hypoxemia, normal left ventricular function, and fever. Symptoms typically occur within 1 to 6 hours after treatment.

Monitor patients for pulmonary adverse reactions. If TRALI is suspected, perform appropriate tests for the presence of anti-neutrophil and anti-HLA antibodies in both the product and patient serum. TRALI may be managed using oxygen therapy with adequate ventilatory support.

5.7 Transmissible Infectious Agents

Because GAMMAGARD S/D is made from human blood and may carry a risk of transmitting infectious agents, e.g., viruses the variant Creutzfeldt-Jakob disease (vCJD) agent and theoretically, the Creutzfeldt-Jakob disease (CJD) agent. This also applies to unknown or emerging viruses and other pathogens.

All infections thought by a physician possibly to have been transmitted by this product should be reported by the physician or other healthcare provider to Takeda Pharmaceuticals U.S.A., Inc. at 1-877-TAKEDA-7 (1-877-825-3327) (in the U.S.) or FDA at 1-800-FDA-1088 or www.fda.gov/medwatch. The physician should discuss the risks and benefits of this product with the patient.

5.8 Hyperproteinemia, Increased Serum Viscosity, and Alterations in Serum Sodium Levels

Hyperproteinemia and increased serum viscosity may occur in patients receiving GAMMAGARD S/D. Alterations in serum sodium levels, such as hypernatremia acutely, or pseudohyponatremia after equilibration of the sodium, may occur with the administration of GAMMAGARD S/D.

The amount of sodium in the product may add materially to the recommended daily allowance of dietary sodium for patients on a low sodium diet. In these patients, calculate the amount of sodium from the product and use it when determining dietary sodium intake. GAMMAGARD S/D contains approximately 0.85% NaCl or approximately 3340 mg sodium/liter at a 5% concentration. A 70 kg patient receiving 1g/kg (1.4 L) of the product would receive 4676 mg of sodium.

5.9 Monitoring: Laboratory Tests

- Monitor renal function and urine output in patients at increased risk of developing acute renal failure. Assess renal function, including measurement of BUN and serum creatinine, before the initial infusion of GAMMAGARD S/D and at appropriate intervals thereafter.^10
- Assess baseline blood viscosity in patients at risk for hyperviscosity, including those with cryoglobulins, fasting chylomicronemia/markedly high triacylglycerols (triglycerides), or monoclonal gammopathies because of the potentially increased risk of thrombosis.
- If signs or symptoms of hemolysis are present after an infusion of GAMMAGARD S/D, perform appropriate laboratory testing for confirmation.
- If TRALI is suspected, perform appropriate tests for the presence of anti-neutrophil antibodies and anti-HLA antibodies in both the product and patient's serum.

5.10 Interference with Laboratory Tests

- After infusion of IgG, the transitory rise of the various passively transferred antibodies in the patient's blood may yield false positive serological testing results, with the potential for misleading interpretation. Passive transmission of antibodies to erythrocyte antigens (e.g., A, B, and D) may cause a positive direct or indirect antiglobulin (Coombs') test.
- Administration of GAMMAGARD S/D can lead to false positive readings in assays that depend on detection of beta-D-glucans for diagnosis of fungal infections; this may persist during the weeks following infusion of the product.

6 ADVERSE REACTIONS

The most common adverse reactions reported in ≥ 5% of clinical trial subjects occurring during or within 48 hours of an infusion were headache, nausea, chills, asthenia (fatigue), pyrexia, upper abdominal pain, diarrhea, back pain, hyperhidrosis, and flushing.

There were no serious adverse events that were attributed to GAMMAGARD S/D in the clinical trials.

In postmarketing surveillance, serious adverse reactions reported with GAMMAGARD S/D were anaphylaxis, acute renal failure, myocardial infarction, cerebral vascular accident, transient ischemic attack, deep vein thrombosis, pulmonary embolism, aseptic meningitis, acute hemolysis, and TRALI.

6.1 Clinical Trials Experience

Because clinical trials are conducted under widely varying conditions, adverse reaction rates observed in the clinical trials of a drug cannot be directly compared to rates in the clinical trials of another drug and may not reflect the rates observed in clinical practice.

Primary Immunodeficiency (PI)

In 17 patients receiving GAMMAGARD (5% solution) for 56 to 77 months, 12 (71%) were adults, and 5 (29%) were children (16 years or younger).^3 Adverse reactions are those adverse events (AEs) that were deemed by the investigators as causally related to the infusion of GAMMAGARD. Twenty-one adverse reactions occurred in 6 of the 17 subjects with a total of 341 infusions (6%). There was one death in a woman from a cerebral vascular hemorrhage secondary to thrombocytopenia that was considered unrelated to study product. Of the 5 subjects who received an infusion with 600 mg/kg at a rate of 0.3 g/kg/hour, two subjects experienced adverse reactions, with an adverse reaction rate of 40%.

The adverse reactions that occurred in ≥ 5% of subjects during or within 48 hours of infusion are listed in Table 2.

Table 2 Adverse Reactions that Occurred in ≥ 5% of Subjects During or Within 48 Hours of Infusion
Adverse Reaction | By Subjects (%) Total number of subjects: 17 | By Infusions (%) Total number of infusions: 341
Headache | 3 (17.6) | 3 (0.9)
Chills | 2 (11.8) | 6 (1.8)
Backache | 2 (11.8) | 2 (0.6)
Emesis | 1 (5.9) | 1 (0.3)
Flushing | 1 (5.9) | 1 (0.3)
Fatigue | 1 (5.9) | 4 (1.2)
Dizziness | 1 (5.9) | 1 (0.3)

In a double-blind, crossover study, 36 subjects with PI were treated for 6 months with GAMMAGARD S/D and 6 months with Gamimune N. One hundred AEs were considered to be possibly or probably related to treatment with GAMMAGARD S/D. Of these, 72 were mild, 24 were moderate, and 4 were severe. The numbers and percentages of AEs were similar for GAMMAGARD S/D and Gamimune N. There were no deaths during the study. The adverse reactions that occurred during GAMMAGARD S/D treatment in ≥ 5% of subjects in the study are shown in Table 3.

Table 3 Adverse Reactions that Occurred in ≥ 5% of Subjects Treated with GAMMAGARD S/D
Adverse Reactions | By Subject (%) Total number of subjects: 36 | By Infusion (%) Total number of infusions: 211
Headache | 11 (30.6) | 23 (10.9)
Nausea | 8 (22.2) | 14 (6.6)
Chills | 7 (19.4) | 14 (6.6)
Fatigue | 4 (11.1) | 11 (5.2)
Pyrexia | 4 (11.1) | 6 (2.8)
Upper Abdominal Pain | 3 (8.3) | 3 (1.4)
Diarrhea | 3 (8.3) | 3 (1.4)
Back Pain | 3 (8.3) | 4 (1.9)
Infusion Site Pain | 2 (5.6) | 3 (1.4)
Hyperhidrosis | 2 (5.6) | 4 (1.9)
Flushing | 2 (5.6) | 2 (1.0)

In 10 subjects who participated in a PK crossover study of GAMMAGARD and GAMMAGARD S/D, 5 adverse reactions were reported to be associated with the total 28 infusions (17.5%). Three of the adverse reactions were associated with 10 GAMMAGARD infusions and 2 were associated with 18 GAMMAGARD S/D infusions. Two subjects withdrew from the study. One subject developed a recurrence of chronic cellulitis and was hospitalized, but the event was not considered to be related to study drug. The other subject withdrew because of moderate severe adverse reactions including chills, anxiety, and increased temperature after infusion of GAMMAGARD.

Adverse reactions that occurred in the PK study and in the safety study are shown in Table 4.

Table 4 Adverse Reactions that Occurred During or Within 48 Hours of an Infusion of GAMMAGARD S/D
Event | By Infusion (%) Total number: 394
Headache | 20 (5.1)
Chills | 11 (2.7)
Elevated Temperature | 7 (1.8)
Nausea | 6 (1.5)
Emesis | 5 (1.3)
Hypertension | 4 (1.0)
Fatigue | 4 (1.0)
Flushing | 4 (1.0)
Leg Cramps | 3 (0.8)
Flu-Like Symptoms | 2 (0.5)
Exanthema | 2 (0.5)
Loss of Appetite | 2 (0.5)
Anxiety | 1 (0.3)
Backache | 1 (0.3)
Urticaria | 1 (0.3)

The tolerability and viral safety of GAMMAGARD S/D were evaluated in a study of 38 subjects treated with GAMMAGARD S/D for an average of 7.7 months. Adverse reactions were reported from 20 of the 38 subjects (52.6%) in 50 of the total 394 infusions (12.7%) during or within 48 hours of an infusion. Twenty-four (48%) of the adverse reactions occurred in 3 subjects and 26 occurred in the other 35 subjects in 350 infusions. No subject withdrew during the study. Five subjects had a transient borderline elevation in liver enzyme (AST). No subject developed a positive serologic response to hepatitis C or HIV. There were no other significant laboratory abnormalities.

The adverse experiences of GAMMAGARD S/D reconstituted as a 10% solution and the maximal tolerated infusion rate were examined in a post-marketing study of 27 subjects. Local pain and/or irritation occurred in 42 of the total 276 infusions (15.2%). Ninety percent of the reactions occurred when the patients received the 10% solution compared to the 5% control. These local reactions tended to be more common following hand vein infusions and their incidence may be reduced by infusions via the antecubital vein. Application of a warm compress to the infusion site alleviated local symptoms. Twenty-six subjects achieved the maximal infusion rate of 8 mL/kg/hour with the GAMMAGARD S/D reconstituted to a 10% solution.

B-cell Chronic Lymphocytic Leukemia (CLL)

In the study of 81 patients with B-cell CLL, the incidence of adverse reactions following GAMMAGARD infusions was approximately 1.3% compared to the rate of the placebo (normal saline) group which was 0.6%.^3 There were 23 adverse reactions associated with the 1235 infusions in the study. Sixteen of the adverse reactions occurred in the GAMMAGARD group (1.6%) and 7 in the control group (0.6%). The most common reactions were fever and chills. Sleepiness was noted during 4 infusions. One subject had a myocardial infarction which was considered to be unrelated to the GAMMAGARD. Twenty-four of the subjects did not complete all 17 infusions. Three subjects in each group died during the study, five of whom were due to infection. The other 18 subjects withdrew for reasons unrelated to the treatment.

Idiopathic Thrombocytopenic Purpura (ITP)

During the clinical study of GAMMAGARD for the treatment of ITP, headache occurred in 12 of 16 subjects (75%) and was the only adverse reaction reported. Of these 12 subjects, 11 had chronic ITP (9 adults, 2 children), and one child had acute ITP. Oral antihistamines and analgesics alleviated the symptoms and were used as pretreatment for those subjects requiring additional IGIV therapy.

Kawasaki Syndrome

In a study of 51 subjects with Kawasaki syndrome, no hypersensitivity reactions (urticaria, bronchospasm or generalized anaphylaxis) were reported in subjects receiving either a single 1g/kg dose or 400 mg/kg of GAMMAGARD for four consecutive days. Adverse reactions, including chills, flushing, cramping, headache, hypotension, nausea, rash, and wheezing, were reported with both dose regimens. These adverse reactions occurred in 7 of the 51 (13.7%) subjects associated with 7 of the total 129 (5.4%) infusions. Of the 25 subjects who received a single 1 g/kg dose, 4 subjects (16%) experienced adverse reactions. Of the 26 subjects who received 400 mg/kg/day over 4 days, 3 (11.5%) experienced adverse reactions.

6.2 Postmarketing Experience

Because adverse reactions are reported voluntarily post-approval from a population of uncertain size, it is not always possible to reliably estimate their frequency or establish a causal relationship to product exposure.

The following adverse reactions have been reported during postmarketing use of GAMMAGARD S/D (Table 5).

Table 5 Adverse Reactions from Postmarketing Experience
Blood and Lymphatic System Disorders | Anemia, hemolysis, lymphadenopathy, thrombocytopenia
Immune System Disorders | Anaphylactic shock, anaphylactic/anaphylactoid reaction, hypersensitivity
Psychiatric Disorders | Restlessness
Nervous System Disorders | Aseptic meningitis, cerebrovascular accident, transient ischemic attack, seizures, dizziness, migraine, paresthesia, syncope, tremor
Eye Disorders | Retinal vein thrombosis, eye pain, photophobia, visual disturbance
Cardiac Disorders | Myocardial infarction, cyanosis, tachycardia, bradycardia
Vascular Disorders | Vena cava thrombosis, arterial thrombosis, deep vein thrombosis, hypotension, hypertension, pallor, thrombophlebitis
Respiratory, Thoracic And Mediastinal Disorders | Pulmonary embolism, pulmonary edema, bronchospasm, wheezing, cough, hyperventilation, hypoxia, throat tightness
Gastrointestinal Disorders | Abdominal pain, dyspepsia
Hepatobiliary Disorders | Non-infectious hepatitis
Skin and Subcutaneous Tissue Disorders | Angioedema, dermatitis, erythema, rash
Musculoskeletal And Connective Tissue Disorders | Arthralgia, myalgia
Renal and Urinary Disorders | Renal failure
General Disorders And Administration-Site Conditions | Infusion site reaction, asthenia, edema, rigors
Investigations | Positive direct Coombs test

In addition to the events listed above, the following events have been identified for IGIV products in general:

Renal | Osmotic nephrosis
Respiratory | Cyanosis, apnea, acute respiratory distress syndrome (ARDS)
Integumentary | Bullous dermatitis, epidermolysis, erythema multiforme, Stevens-Johnson syndrome
Cardiovascular | Cardiac arrest, vascular collapse
Neurological | Coma, loss of consciousness
Hematologic | Pancytopenia
Gastrointestinal | Hepatic dysfunction

7 DRUG INTERACTIONS

Admixtures of GAMMAGARD S/D with other drugs and intravenous solutions have not been evaluated. It is recommended that GAMMAGARD S/D be administered separately from other drugs or medications which the patient may be receiving. Do not mix the product with human IGIV products from other manufacturers.

Passive transfer of antibodies may transiently impair the immune responses to live attenuated vaccines, such as measles, mumps, rubella, and varicella. Inform the immunizing physician of recent therapy with GAMMAGARD S/D so that appropriate precautions can be taken.

8 USE IN SPECIFIC POPULATIONS

8.1 Pregnancy

Risk Summary

Animal reproduction studies have not been conducted with GAMMAGARD S/D. It is not known whether GAMMAGARD S/D can cause fetal harm when administered to a pregnant woman or can affect reproduction capacity. Immunoglobulins cross the placenta from maternal circulation increasingly after 30 weeks of gestation. GAMMAGARD S/D should be given to a pregnant woman only if clearly needed.

The background risk of major birth defects and miscarriage for the indicated population is unknown. In the U.S. general population, the estimated background risk of major birth defects and miscarriage in clinically recognized pregnancies is 2-4% and 15-20%, respectively.

8.2 Lactation

Risk Summary

There is no information regarding the presence of GAMMAGARD S/D in human milk, its effects on the breastfed infant or its effects on milk production. The developmental and health benefits of breastfeeding should be considered along with the mother's clinical need for GAMMAGARD S/D and any potential adverse effects on the breastfed infant from GAMMAGARD S/D or from the underlying maternal condition.

8.4 Pediatric Use

Clinical studies for the treatment of PI did not include sufficient numbers of subjects aged 16 and younger to determine whether they respond differently from adults. Five children under the age of 16 were treated in the initial trial of GAMMAGARD. The mean age of subjects in the phase 4 study was 17.8 years (range 1.7 to 55.3).

Efficacy and safety of GAMMAGARD S/D in pediatric patients with chronic ITP has not been established.

Efficacy and safety of GAMMAGARD S/D in pediatric patients with Kawasaki disease has been established. Virtually all patients treated for Kawasaki disease were less than 5 years of age, with approximately 20% under the age of 1 year.

8.5 Geriatric Use

Limited information is available for the geriatric use. Clinical studies of GAMMAGARD S/D for the treatment of PI did not include sufficient numbers of subjects aged 65 and over to determine whether they respond differently from younger subjects. When administering GAMMAGARD S/D to patients age 65 and over who are at increased risk for developing thromboembolic events or renal insufficiency, do not exceed the recommended dose and administer GAMMAGARD S/D at the minimum infusion rate practicable [see Boxed Warning, Warnings and Precautions(5.2, 5.4) and Dosage and Administration (2.2)].

10 OVERDOSAGE

Overdose may lead to fluid overload or hyperviscosity. Patients at particular risk for complications of fluid overload or hyperviscosity include elderly patients and patients with cardiac or renal impairment.

11 DESCRIPTION

GAMMAGARD S/D, Immune Globulin Intravenous (Human), IgA less than 1 µg/mL in a 5% Solution (IgA < 1 µg/mL), is GAMMAGARD S/D selected to have an IgA concentration of less than 1 µg/mL of IgA in a 5% solution. GAMMAGARD S/D is a solvent/detergent treated, sterile, freeze-dried preparation of purified immunoglobulin G (IgG) derived from large pools of human plasma. IgG preparations are purified from plasma pools using a modified Cohn-Oncley cold ethanol fractionation process, as well as cation and anion exchange chromatography steps. The distribution of IgG subclasses present in this product is similar to that in normal plasma. The Fc portion is maintained intact. When reconstituted with the total volume of diluent (Sterile Water for Injection, USP) supplied and reconstituted to 5% solution, the product contains approximately 50 mg/mL of protein, of which at least 90% is gamma globulin. GAMMAGARD S/D contains < 1 µg/mL of IgA in a 5% solution and IgM is present in trace amounts. GAMMAGARD S/D contains all of the IgG antibody activities which are present in the donor population.

The product, after reconstituted to 5% solution, contains a physiological concentration of sodium chloride (approximately 8.5 mg/mL) and has a pH of 6.8 ± 0.4. Stabilizing agents and additional components are present in the following maximum amounts for a 5% solution: 3 mg/mL Albumin (Human), 22.5 mg/mL glycine, 20 mg/mL glucose, 2 mg/mL polyethylene glycol (PEG), 1 µg/mL tri-n-butyl phosphate, 1 µg/mL octoxynol 9, and 100 µg/mL polysorbate 80. GAMMAGARD S/D contains no preservative.

To prepare a 10% (100 mg/mL) solution for infusion, add half the volume of diluent, as described in Dosage and Administration (2.1). The content of the stabilizing agents and other components, including IgA, for the 10% solution will be doubled compared to the 5% solution.

Screening against potentially infectious agents in the product begins with the donor selection process and continues throughout plasma collection and plasma preparation. Each individual plasma donation used in the manufacture of GAMMAGARD S/D is collected only at FDA approved blood establishments and is tested by FDA licensed serological tests for hepatitis B surface antigen (HBsAg), and for antibodies to human immunodeficiency virus (HIV-1/HIV-2) and hepatitis C virus (HCV) in accordance with U.S. regulatory requirements. As an additional safety measure, mini-pools of the plasma are tested for the presence of HIV-1 and HCV by FDA licensed nucleic acid testing (NAT) and found negative.

The manufacturing process includes treatment with an organic solvent/detergent mixture^12,13, composed of tri-n-butyl phosphate, octoxynol 9 and polysorbate 80. The GAMMAGARD S/D manufacturing process provides for viral reduction in in vitro studies. These studies, summarized in Table 6 demonstrate virus clearance during GAMMAGARD S/D manufacturing using human immunodeficiency virus, Type 1 (HIV-1), as the relevant virus and model for HIV-2; bovine viral diarrhea virus (BVDV), a model virus for enveloped RNA viruses such as hepatitis C virus (HCV); pseudorabies virus (PRV), a generic model virus for enveloped DNA viruses such as hepatitis B virus (HBV); encephalomyocarditis virus (EMCV), a model for non-enveloped RNA viruses such as hepatitis A virus (HAV); HAV; and mice minute virus (MMV), a model for small non-enveloped DNA viruses such as human parvovirus B19 (B19V). These reductions are achieved through partitioning and inactivation during cold ethanol fractionation, and the solvent/detergent treatment.

Table 6 In Vitro Virus Clearance During GAMMAGARD S/D Manufacturing
Process Step Evaluated |  | Virus Clearance (log10)
 |  | Enveloped Viruses |  |  | Non- Enveloped Viruses
 |  | HIV-1 | BVDV | PRV | EMCV | HAV | MMV
Step 1: | Processing of Cryo-Poor Plasma to Fraction I+II+III Precipitate | 5.6 | 0.6 [These values are not included in the computation of the cumulative reduction of virus since the virus clearance is within the variability limit of the assay (≤1.0).] | 1.0 | NT | 0.5 | NT
Step 2-3: | Processing of Resuspended Suspension A Precipitate to Suspension B Cuno 70 Filtrate | > 5.7 | 2.6 | > 5.2 | 5.0 | > 5.2 | > 5.3
Step 4: | Solvent/Detergent Treatment | >5.5 | >6.2 | >4.9 | NA | NA | NA
Cumulative Reduction of Virus (log10) |  | >16.8 | >8.8 | >10.1 | 5.0 | > 5.2 | > 5.3
NA Not Applicable. Solvent/detergent treatment does not affect non- enveloped viruses.
NT Not Tested.

12 CLINICAL PHARMACOLOGY

12.1 Mechanism of Action

GAMMAGARD S/D, Immune Globulin Intravenous (Human), supplies a broad spectrum of opsonizing and neutralizing IgG antibodies against a wide variety of bacterial and viral agents. GAMMAGARD S/D also contains a spectrum of antibodies capable of reacting with cells such as erythrocytes. The role of these antibodies and the mechanisms of action of IgG in GAMMAGARD S/D have not been fully elucidated.

12.3 Pharmacokinetics

Following infusion, IGIV products show a biphasic decay curve. The initial (α) phase is characterized by an immediate post-infusion peak in serum IgG and is followed by rapid decay due to equilibration between the plasma and extravascular fluid compartments. The second (β) phase is characterized by a slower and constant rate of decay. As a class, IgG survives longer in vivo than other serum proteins. Peak levels of IgG are reached within 30 minutes after an intravenous infusion of GAMMAGARD S/D. In previous studies, where radio-labeled IgG was injected to subjects, the IgG half-life was 21 to 25 days in healthy individuals or 17.7 to 37.6 days in immunodeficient patients. The half-life of IgG can vary considerably from person to person, however. In particular, high serum concentrations of IgG and hypermetabolism associated with fever and infection have been seen to coincide with a shortened half-life of IgG.

The pharmacokinetics of GAMMAGARD S/D were evaluated in 15 subjects with PI, 10 of whom were previously treated. In the previously treated subjects, the half-life of GAMMAGARD S/D was approximately 37.7 ± 15 days compared to 34.1 ± 15.7 days for GAMMAGARD. The half-lives of the IgG subclasses were similar, ranging from 28.1 ± 11.2 days for IgG4 to 42.3 ± 26.6 days for IgG1. The half-life of pneumococcal antibody in these subjects was 41.4 ± 28.5 days. Pharmacokinetics did not differ between the previously licensed IGIV and GAMMAGARD S/D formulations administered to the previously treated patients. The pharmacokinetics of the GAMMAGARD S/D formulation in previously untreated patients were not significantly different from the results obtained in previously treated patients. The mean trough IgG concentration in the previously untreated patients was 1186 ± 614 mg/dL and the peak post-infusion concentration was 1859 ± 872 mg/dL. The mean dose was 460 ± 194 mg/kg.

14 CLINICAL STUDIES

Clinical studies were conducted with lots of GAMMAGARD S/D containing IgA < 2.2 µg/mL. No clinical studies have been specifically conducted using only lots with IgA content of < 1 µg/mL.

Primary Immunodeficiency (PI)

Intravenous use of GAMMAGARD was initially evaluated in a study of 17 subjects with PI. Twelve (71%) were adults and 5 (29%) were children 16 years or younger. Six subjects received a series of 5 infusions at 4-week intervals, with the starting infusion dose of 100 mg/kg and then increased to 200, 300, and 400 mg/kg at rates of 0.1 to 0.2 mg/kg/hour. Five of the 6 subjects completed the 5 infusions and received another 6 monthly infusions with the following doses each administered twice: 200-400 mg/kg at 0.1 to 0.2 g/kg/hour, 400 mg/kg at 0.1 to 0.4 g/kg/hour and 400-800 mg/kg at 0.1 to 0.4 g/ kg/hour. Then all of the 17 subjects received GAMMAGARD at 400 mg/kg every 4 weeks at a rate of 0.1 to 0.4 g/kg/hour. Fifteen of the subjects were treated for 56 to 77 weeks in this study. There were no instances of pneumonia or other infections that would qualify as an acute bacterial infection. The overall rate of non-serious bacterial infections was 4.4 per subject per year.

In a study of 15 subjects with PI to compare the pharmacokinetics of GAMMAGARD S/D with GAMMAGARD, the subjects received a total of 28 infusions, half with GAMMAGARD S/D and half with GAMMAGARD. Five systemic AEs were reported during the study and 2 occurred with GAMMAGARD S/D treatment. The study then enrolled an additional 38 patients with the diagnosis of PI (8), ITP (13), CVID (5), CLL (2) and other miscellaneous diseases (3) to evaluate acute tolerability and the viral safety of GAMMAGARD S/D.

The mean age of the subjects was 12 years old (range 0.7 to 57.2 years); 17 were males and 21 were females. The subjects received an average of 10 (range 1-22) infusions over an average of 7.7 months (range 0.3-11 months). A total of 394 infusions were administered and all were completed. The average dose was 460 mg/kg (range: 188-1110 mg/kg). Incidence of infections was not recorded, although one subject had a recurrence of chronic cellulitis. Adverse events and viral safety data were analyzed [see Adverse Reactions(6)].

GAMMAGARD S/D was compared to Gamimune N in a double-blind, crossover study of 36 PI subjects. The mean age of subjects was 17.8 years (range 1.7 to 55.3 years); 22 subjects were male and 14 were female. Eighteen were naïve to IGIV therapy. Each subject received 6 infusions of both products. There were a total of 211 GAMMAGARD S/D infusions and 210 Gamimune N infusions. The dose of GAMMAGARD S/D administered was 300-600 mg/kg every 14 to 28 days for previously untreated subjects and the same as their pre-study dose and frequency for previously treated subjects. The infusions were started at 1.0 mL/kg/hour and increased every 30 minutes to a maximum of 4.8 mL/kg/hour as tolerated. The mean dose administered for both products was 440 mg/kg. The mean infusion rate was 2.35 ± 0.54 mL/kg/hour for GAMMAGARD S/D and 2.33 ± 0.71 for Gamimune N. Two subjects withdrew from the study. One subject was pregnant, and the other subject was withdrawn by his parents after the eighth infusion for reasons other than adverse events.

The use of GAMMAGARD S/D as a 10% solution and the maximal rate of infusion were evaluated in a postmarketing study of 27 subjects with PI. Subjects were treated with GAMMAGARD S/D at 400 mg/kg every 4 weeks for up to 12 months. Each subject received an initial infusion of GAMMAGARD S/D 5% solution at 4 mL/kg/hour. Subsequently, the concentration was increased to 7.5% and then to 10% as tolerated. Thereafter, the infusion rate was gradually increased to a maximal 8 mL/kg/hour as tolerated. There were 276 infusions administered and 26 of the 27 subjects were able to reach the maximum infusion rate and concentration.

B-cell Chronic Lymphocytic Leukemia (CLL)

The efficacy of GAMMAGARD in reducing bacterial infections of B-cell CLL patients has been demonstrated in a double-blind, placebo-controlled trial of 81 subjects.^4 Subjects were treated with 400 mg/kg/dose of GAMMAGARD or saline solution every 3 weeks for a total of 17 infusions. Forty-one subjects received GAMMAGARD and 40 subjects received saline. The infection outcomes, including the frequency of bacterial/viral/fungal infections, mean time to first bacterial infections, were compared between the two groups and are shown in Table 7.

Table 7 Infection Outcomes of 81 B-Cell CLL Subjects with GAMMAGARD or Placebo
Outcome | GAMMAGARD S/D | Placebo | Significance P value
Number of subjects | 41 | 40 | -
Frequency of bacterial infections | 56.1% | 105% | 0.01
Mean time to first bacterial infection | > 365 | 192 | 0.026
Total Bacterial Infections | 23 | 42 | 0.01
Total Viral Infections | 40 | 37 | 0.65
Fungal or Candida infection | 3 | 2 | -
Patients free of any infection | 13 | 11 | 0.68

Patients receiving GAMMAGARD had fewer infections with Streptococcus pneumoniae and Haemophilus influenza, but the incidence of other gram negative infections was similar.

Idiopathic Thrombocytopenic Purpura (ITP)

The efficacy of GAMMAGARD has been demonstrated in a clinical study involving 16 patients: thirteen had chronic ITP (11 adults, 2 children), and 3 had acute ITP (one adult, 2 children). All 16 patients (100%) demonstrated a rise in platelet count to a level greater than 40,000/mm^3 following the administration of GAMMAGARD. Ten of the 16 patients (62.5%) exhibited a platelets rise to greater than 80,000 /mm^3. Of these 10 patients, 7 had chronic ITP (5 adults, 2 children), and 3 had acute ITP (one adult, 2 children).

Increase in platelet count to greater than 40,000/mm^3 occurred after a single 1 g/kg infusion of GAMMAGARD in 8 patients with chronic ITP (6 adults, 2 children), and in 2 patients with acute ITP (one adult, one child). A similar response was observed after two 1 g/kg infusions in 3 adult patients with chronic ITP, and one child with acute ITP. The remaining 2 adult patients with chronic ITP received more than two 1 g/kg infusions before achieving a platelet count greater than 40,000/mm^3. The rise in platelet count occurred within 5 days. However, this rise was transient and not considered curative. Platelet count rises lasted 2 to 3 weeks, with a range of 12 days to 6 months. It should be noted that childhood ITP may resolve spontaneously without treatment.

Kawasaki Syndrome

The efficacy of GAMMAGARD S/D for reducing the incidence of coronary artery aneurysm in patients with Kawasaki syndrome has been demonstrated in a clinical study of 44 patients.^7 The incidence of coronary artery aneurysm in patients with Kawasaki syndrome receiving GAMMAGARD either at a single dose of 1 g/kg (n=22) or at a dose of 400 mg/kg for four consecutive days (n=22), beginning within seven days of onset of fever, was 3/44 (6.8%). This was significantly different (p=0.008) from a comparable group of patients that received aspirin only in previous trials and of whom 42/185 (22.7%) developed coronary artery aneurysms. All patients in the GAMMAGARD trial received concomitant aspirin therapy and none experienced hypersensitivity reactions (urticaria, bronchospasm or generalized anaphylaxis).

15 REFERENCES

1. Orange JS, Hossny EM, Weiler CR, Ballow M, Berger M, Bonilla FA, Buckley R, Chinen J, El-Gamal Y, Mazer BD, Nelson Jr. RP, Patel DD, Secord E, Sorenson RU, Wasserman RL, Cunningham-Rundles C, Use of Intravenous Immunoglobulin in Human Disease: A Review of Evidence by Members of the Primary Immunodeficiency Committee of the American Academy of Allergy, Asthma, and Immunology. J Allergy Clin Immunol 2006; 117:S525-53.
2. Bonilla FA, Bernstein IL, Khan DA, Ballas ZK, Chinen J, Frank MM, et al. Practice parameter for the diagnosis and management of primary immunodeficiency. Ann Allergy Asthma Immunol. 2005; 94(suppl 1):S1-63.
3. Ochs HD, Lee ML, Fischer SH, et al. Efficacy of a New Intravenous Immunoglobulin Preparation in Primary Immunodeficient Patients. Clinical Therapeutics. 1987; 9:512-522.
4. Cooperative Group for the Study of Immunoglobulin in Chronic Lymphocytic Leukemia: Intravenous immunoglobulin for the prevention of infection in Chronic Lymphocytic Leukemia: A randomized, controlled clinical trial. N Eng J Med. 1988; 319:902-907.
5. Newburger J, Takahashi M, Burns JG, et al. The Treatment of Kawasaki Syndrome with Intravenous Gamma Globulin. New England Journal of Medicine. 1986; 315:341-347.
6. Eijkhout HW, Der Meer JW, Kallenbert CG, et al. The effect of two different dosages of intravenous immunoglobulin on the incidence of recurrent infections in patients with primary hypogammaglobulinemia. A randomized, double-blind, multicenter crossover trial. Ann Intern Med. 2001; 135:165-174.
7. Barron KS, Murphy DJ, Siverman ED, Ruttenberg HD, Wright GB, Franklin W, Goldberg SJ, Higashino SM, Cox DG, Lee M. Treatment of Kawasaki syndrome: a comparison of two dosage regimens of intravenously administered immune globulin. J Pediatr. 1990; 117:638-644.
8. Engle MA, Fatica NS, Bussel JB, O'Laughlin JE, Snyder MS, Lesser ML. Clinical Trial of Single-Dose Intravenous Gammaglobulin in Acute Kawasaki Disease. AJDC. 1989; 143:1300-1304.
9. Polmar SH, Smith TF, Pirofsky B, Cox DG, Rechtman D. Rapid infusion of intravenous immunoglobulin in patients with primary immunodeficiency disease. J Allergy Clin Immunol. 1992; 69:166.
10. Pierce LR, Jain N. Risks associated with the use of intravenous immunoglobulin. Transfusion Med Rev. 2003; 17:241-251.
11. Daw Z, Padmore R, Neurath D, Cober N, Tokessy M, Desjardins D, et al. Hemolytic transfusion reactions after administration of intravenous immune (gamma) globulin: a case series analysis. Transfusion 2008; 48:1598-601.
12. Horowitz B, Wiebe ME, Lippin A, et al. Inactivation of viruses in labile blood derivatives: I. Disruption of lipid enveloped viruses by tri-n-butyl phosphate detergent combinations. Transfusion. 1985;25:516-522.
13. Prince AM, Horowitz B, Brotman B. Sterilisation of hepatitis and HTLV-III viruses by exposure to tri-n-butyl phosphate and sodium cholate. Lancet. 1986;1:706-710.

16 HOW SUPPLIED/STORAGE AND HANDLING

GAMMAGARD S/D is supplied in single use bottles containing the labeled amount of functionally active IgG. The following presentation of GAMMAGARD S/D is available:

Grams Protein | Kit NDC
5 g | 0944-2656-03
10 g | 0944-2658-04

Each bottle of GAMMAGARD S/D is furnished with a suitable volume of Sterile Water for Injection, USP, a transfer device and an administration set which contains an integral airway and a 15 micron filter.

STORAGE AND HANDLING

Store GAMMAGARD S/D at a temperature not to exceed 25ºC (77ºF) for 24 months.

Do not Freeze.

Not made with natural rubber latex.

17 PATIENT COUNSELING INFORMATION

Inform patients to immediately report the following signs and symptoms to their healthcare provider:

- Decreased urine output, sudden weight gain, fluid retention/edema, or shortness of breath [see Warnings and Precautions (5.2)].
- Instruct patients to immediately report symptoms of thrombosis. These symptoms may include pain or swelling of an arm or leg with warmth over the affected area, discoloration of an arm or leg, unexplained shortness of breath, chest pain or discomfort that worsens on deep breathing, unexplained rapid pulse, numbness or weakness on one side of the body [see Warnings and Precautions (5.3)].
- Severe headache, neck stiffness, drowsiness, fever, sensitivity to light, painful eye movements, nausea, and vomiting [see Warnings and Precautions (5.4)].
- Increased heart rate, fatigue, yellowing of the skin or eyes, and dark-colored urine [see Warnings and Precautions (5.5)].
- Trouble breathing, chest pain, blue lips or extremities, fever [see Warnings and Precautions (5.6)].
- Inform patients that GAMMAGARD S/D is made from human blood and may contain infectious agents that can cause disease agents e.g., viruses, the variant Creutzfelt-Jakob disease (vCJD) agent and, theoretically, the Creutzfeldt-Jakob disease (CJD) agent. The risk of GAMMAGARD S/D transmitting an infectious agent has been reduced by screening plasma donors for prior exposure, testing donated plasma, and inactivating or removing certain viruses during manufacturing. Patients should report any symptoms that concern them or that might be caused by infections [see Warnings and Precautions (5.7)].
- Inform patients that GAMMAGARD S/D can interfere with their immune response to live viral vaccines such as measles, mumps, and rubella. Inform patients to notify their healthcare professional of this potential interaction when they are receiving vaccinations [see Drug Interactions (7)].

To enroll in the confidential, industry-wide Patient Notification System, call 1-888-873-2838.

Takeda Pharmaceuticals U.S.A., Inc.
Cambridge, MA 02142
U.S. License No. 1898

GAMMAGARD is a registered trademark of Baxalta Incorporated.
Takeda and are registered trademarks of Takeda Pharmaceutical Company Limited.

©2025 Takeda Pharmaceutical Company Limited. All rights reserved.

GSD351
Revised: 2/2025

PRINCIPAL DISPLAY PANEL - 5 g/96 mL Bottle Label

Store at a temperature not to exceed 25°C (77°F).
Do not freeze.

Read enclosed directions for use, including information
on compatibility under "Dosage and Administration."

The patient and physician should discuss the risks
and benefits of this product.

NDC 0944-2657-07

Takeda Pharmaceuticals U.S.A., Inc.
Cambridge, MA 02142
U.S. License No. 1898

Rx Only

Immune Globulin
Intravenous (Human)

GAMMAGARD® S/D

5g
96mL

Takeda

IgA less than 1 µg/mL in a 5% solution

LE-07-62368

PRINCIPAL DISPLAY PANEL - Kit Carton - 5 g/96 mL

NDC 0944-2656-03

Single-dose container. For intravenous administration only.
Read enclosed directions for use, including information on
compatibility under “Dosage and Administration.”

The patient and physician should discuss the risks and
benefits of this product.

Solvent/Detergent Treated

Rx Only

Immune Globulin
Intravenous (Human)

GAMMAGARD® S/D

5g
96mL

IgA less than 1 µg/mL in a 5% solution

Takeda

PRINCIPAL DISPLAY PANEL - 10 g/192 mL Bottle Label

Store at a temperature not to exceed 25°C (77°F). Do not freeze.

Read enclosed directions for use, including information on compatibility
under "Dosage and Administration."

The patient and physician should discuss the risks and
benefits of this product.

NDC 0944-2659-08

Takeda Pharmaceuticals U.S.A., Inc.
Cambridge, MA 02142
U.S. License No. 1898

Rx Only

Immune Globulin
Intravenous (Human)

GAMMAGARD® S/D

10g
192mL

Takeda

IgA less than 1 µg/mL in a 5% solution

LE-07-62373

PRINCIPAL DISPLAY PANEL - Kit Carton - 10 g/192 mL

NDC 0944-2658-04

Single-dose container. For intravenous administration only.
Read enclosed directions for use, including information on
compatibility under “Dosage and Administration.”

The patient and physician should discuss the risks and
benefits of this product.

Solvent/Detergent Treated

Rx Only

Immune Globulin
Intravenous (Human)

GAMMAGARD® S/D

10g
192mL

IgA less than 1 µg/mL in a 5% solution

Takeda